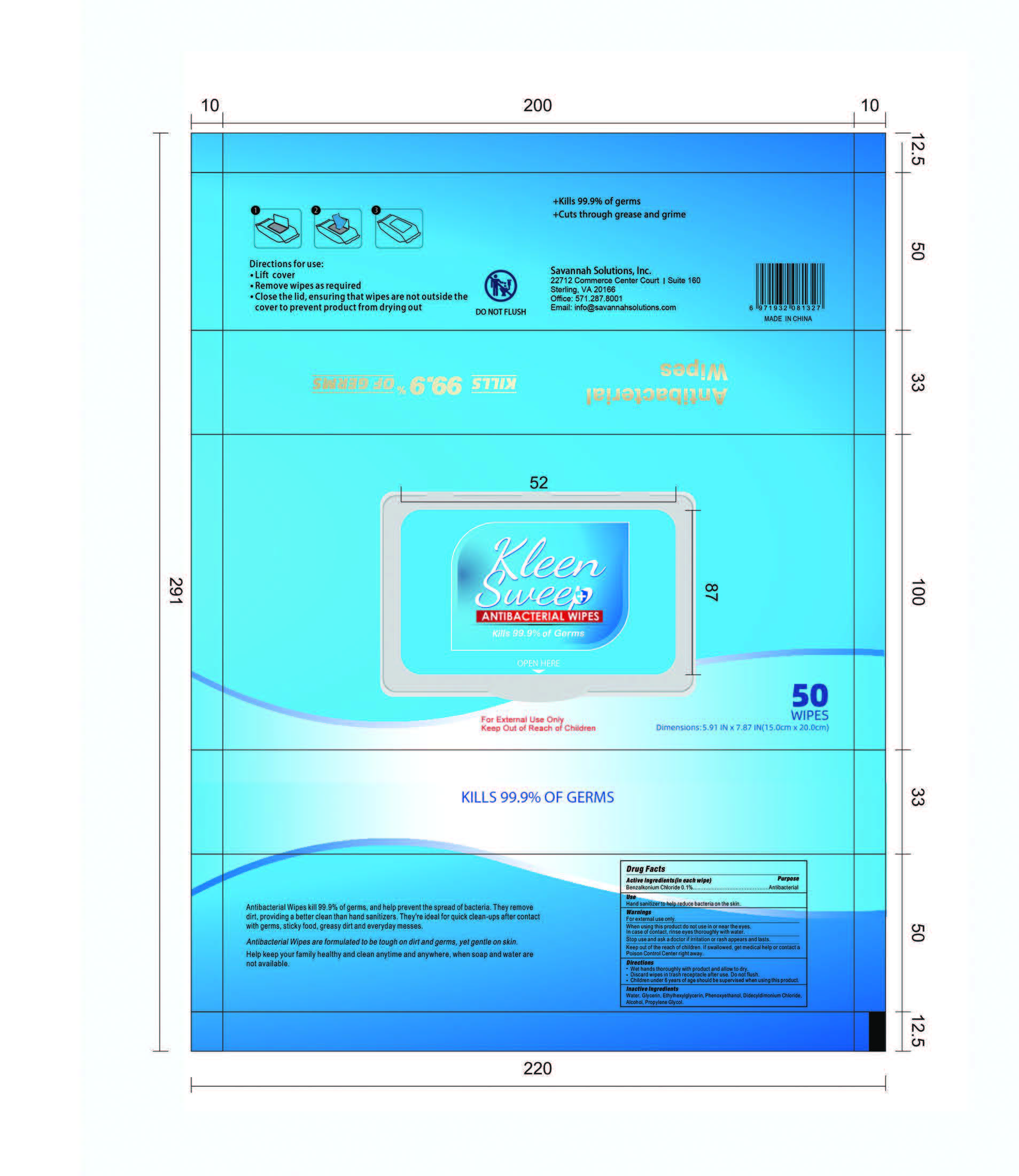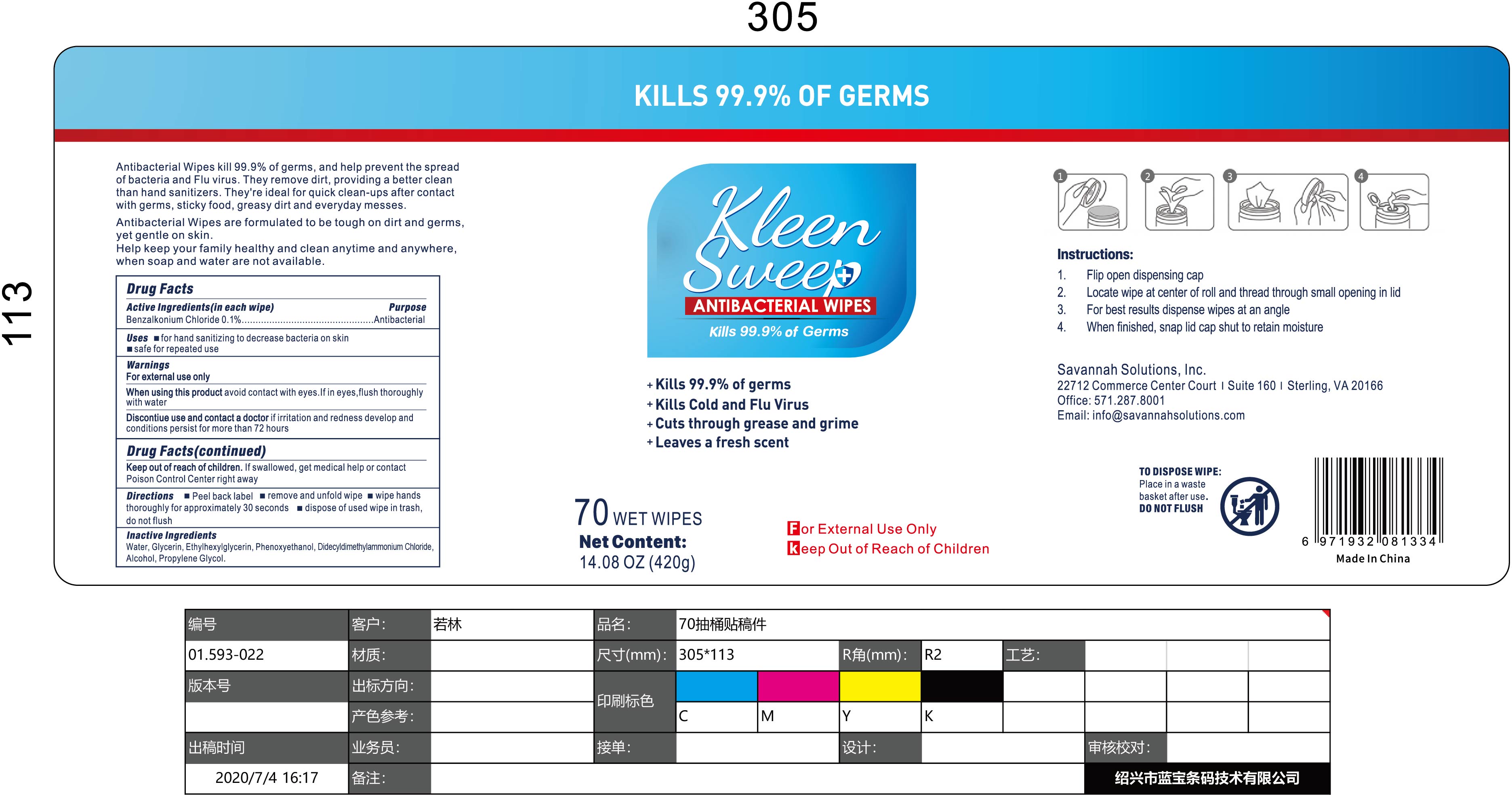 DRUG LABEL: KleenSweep Antibacterial Wipes
NDC: 88888-001 | Form: SWAB
Manufacturer: Savannah Solutions, Inc.
Category: otc | Type: HUMAN OTC DRUG LABEL
Date: 20200620

ACTIVE INGREDIENTS: BENZALKONIUM CHLORIDE 0.1 g/100 g
INACTIVE INGREDIENTS: ALCOHOL; DIDECYLDIMONIUM CHLORIDE; PHENOXYETHANOL; PROPYLENE GLYCOL 2-BEHENATE; GLYCERIN; ETHYLHEXYLGLYCERIN; WATER

KleenSweep Antibacterial Wipes

Antibacterial wipes kill 99.9% of germs and help prevent the spread of bacterial. They remove dirt, providing a better clean than sanitizers. They are ideal for quick clean-ups after contact with germs, sticky food, greasy dirt, and everyday messes. Antibacterial wipes are formulated to be tough on dirt and germs, yet gentle on skin. Help keep your family healthy and clean anytime and anywhere when soap and water are not available.

The ingredients are as follows:

Benzalkonium Chloride :0.1%

Glycerin :0.1%

Ethylhexylglycerin :0.1%

Phenoxyethanol:0.5%

Didecyldimethylammonium Chloride :0.2%

Alcohol:10%

Propylene Glycol :0.1%

Water :88.9%.

Active Ingredient(s)

Benzalkonium Chloride 0.135%

Purpose

Antiseptic, Wipes

Use

Pre-moistened towelettes that contain a sanitizing or disinfecting formula that kill or reduce germs on surfaces and skin

Warnings

Liquid may cause irritation to the eyes. Prolonged or repeated contact may dry skin and cause
irritation and sensitization. Harmful if swallowed.

Do not use

- Skin Contact: Skin irritation is not expected. Should irritation develop, discontinue use. Wash affected skin

thoroughly with soap and water. Get medical attention if irritation or other symptoms develop or persist.

- Eye Contact: Immediately flush eyes with plenty of water for at least 15 minutes, lifting lower and upper eyelids

occasionally. Get medical attention if irritation persists.

- Inhalation: Normal use of this product does not pose an inhalation hazard. Should respiratory tract irritation

develop, discontinue use and remove to fresh air. Get medical attention if irritation or other symptoms persist or
develop.

- Ingestion: Seek medical attention immediately. Never give anything by mouth to an unconscious person. DO

NOT induce vomiting. If vomiting occurs, keep head below hips to prevent aspiration of liquid into lungs.

WHEN USING

- Skin Contact: Skin irritation is not expected. Should irritation develop, discontinue use. Wash affected skin

thoroughly with soap and water. Get medical attention if irritation or other symptoms develop or persist.

- Eye Contact: Immediately flush eyes with plenty of water for at least 15 minutes, lifting lower and upper eyelids

occasionally. Get medical attention if irritation persists.
Inhalation: Normal use of this product does not pose an inhalation hazard. Should respiratory tract irritation
develop, discontinue use and remove to fresh air. Get medical attention if irritation or other symptoms persist or
develop.

- Ingestion: Seek medical attention immediately. Never give anything by mouth to an unconscious person. DO

NOT induce vomiting. If vomiting occurs, keep head below hips to prevent aspiration of liquid into lungs.

STOP USE

Emergency Overview:
WARNING! Liquid may cause irritation to the eyes. Prolonged or repeated contact may dry skin and cause
irritation and sensitization. Harmful if swallowed.

Potential Health Effects
Route of entry: Inhalation, skin contact, eye contact, ingestion.
Skin Contact: Frequent or prolonged contact with skin may cause irritation.
Eye Contact: May cause eye irritation. Symptoms may include stinging, tearing and redness.
Inhalation: Not expected to be a significant exposure route. Vapor or mist may be irritating to mucous
membranes and upper respiratory tract.
Ingestion: May cause gastrointestinal irritation with nausea, vomiting and diarrhea.

Keep out of reach of children. If swallowed, get medical help or contact a Poison Control Center right away.

Directions

- Rub surfaces with wipes and wash your hands afterward

Other information

- Handling: Avoid contact with eyes. Do not eat or drink when handing. Keep ventilation. Use in accordance with

product literature.

- Storage: Store product at room temperature. Keep in a closed package. Protect against physical damage.

Observe all warnings and precautions listed for the product.

Inactive ingredients

Water,Glycerin,Ethylhexylglycerin,Phenoxyethanol,Didecyldimonium Chloride, Alcohol, Propylene Glycol